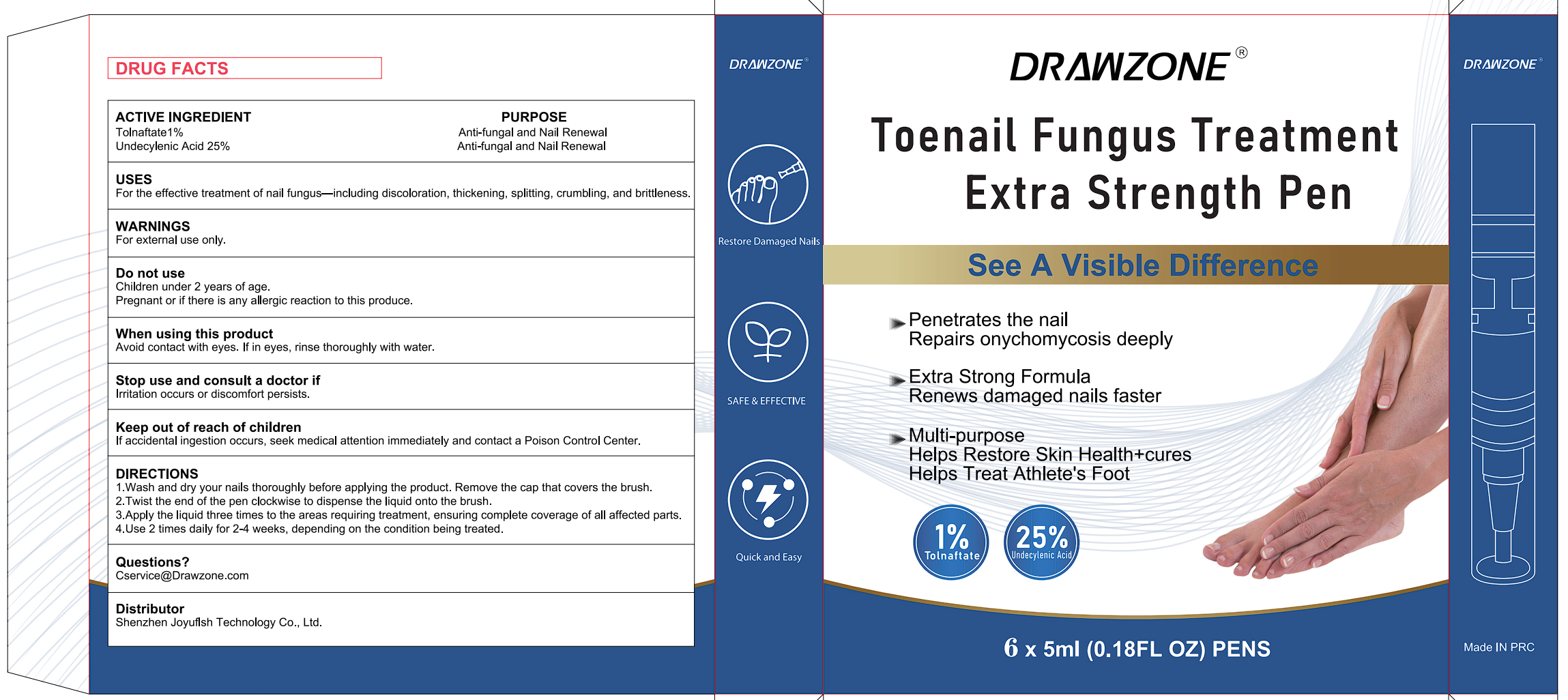 DRUG LABEL: DRAWZONE Toenail Fungus Treatment Pen
NDC: 83766-107 | Form: LIQUID
Manufacturer: Shenzhen Joyuflsh Technology Co.,Ltd.
Category: otc | Type: HUMAN OTC DRUG LABEL
Date: 20250905

ACTIVE INGREDIENTS: UNDECYLENIC ACID 25 g/100 mL; TOLNAFTATE 1 g/100 mL
INACTIVE INGREDIENTS: WATER; TOCOPHEROL; LAUROCAPRAM; ALCOHOL; GLYCERIN; ETHYLHEXYLGLYCERIN; PHENOXYETHANOL; POLYETHYLENE GLYCOL, UNSPECIFIED; PROPYLENE GLYCOL; C12-15 ALKYL LACTATE; SOPHORA FLAVESCENS ROOT; DIMETHICONE

83766-107 DRAWZONE Toenail Fungus Treatment Pen

ACTIVE INGREDIENT

Tolnaftate 1%
UNDECYLENIC ACID 25%

PURPOSE

Anti-fungal and Nail Renewal

INDICATIONS AND USAGE

For the effective treatment of nail fungus-including discoloration, thickening, spliting, crumbling, and britleness

WARNINGS

For external use only.

DO NOT USE

Children under 2 years of age.
Pregnant or if there is any allergic reaction to this produce.

WHEN USING

Avoid contact with eyes. lf in eyes, rinse thoroughly with water.

STOP USE

lrritation occurs or discomfort persists

KEEP OUT OF REACH OF CHILDREN

lf accidental ingestion occurs, seek medical attention immediately and contact a Poison Control Center.

DOSAGE AND ADMINISTRATION

1.Wash and dry your nails thoroughly before applying the product. Remove the cap that covers the brush.
2.Twist the end of the pen clockwise to dispense the liquid onto the brush.
3.Apply the liquid three times to the areas requiring treatment, ensuring complete coverage of all affected parts.
4.Use 2 times daily for 2-4 weeks, depending on the condition being treated.

INACTIVE INGREDIENT

ALCOHOL
POLYETHYLENE GLYCOL
PROPYLENE GLYCOL
DIMETHICONE
C12-15 ALKYL LACTATE
ETHYLHEXYLGLYCERIN
GLYCERIN
LAUROCAPRAM
SOPHORA FLAVESCENS ROOT
TOCOPHEROL
PHENOXYETHANOL
WATER